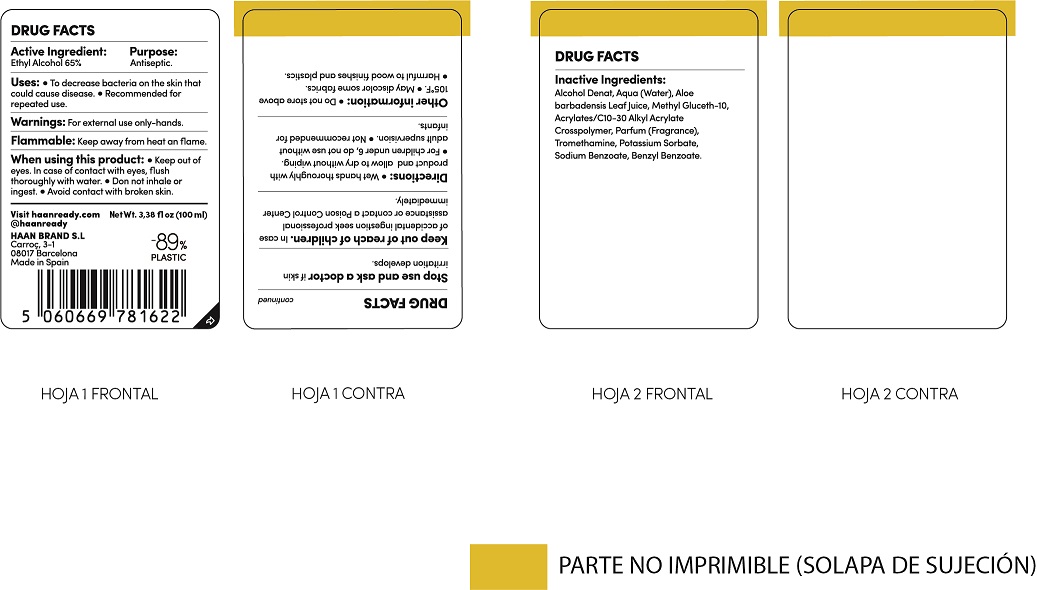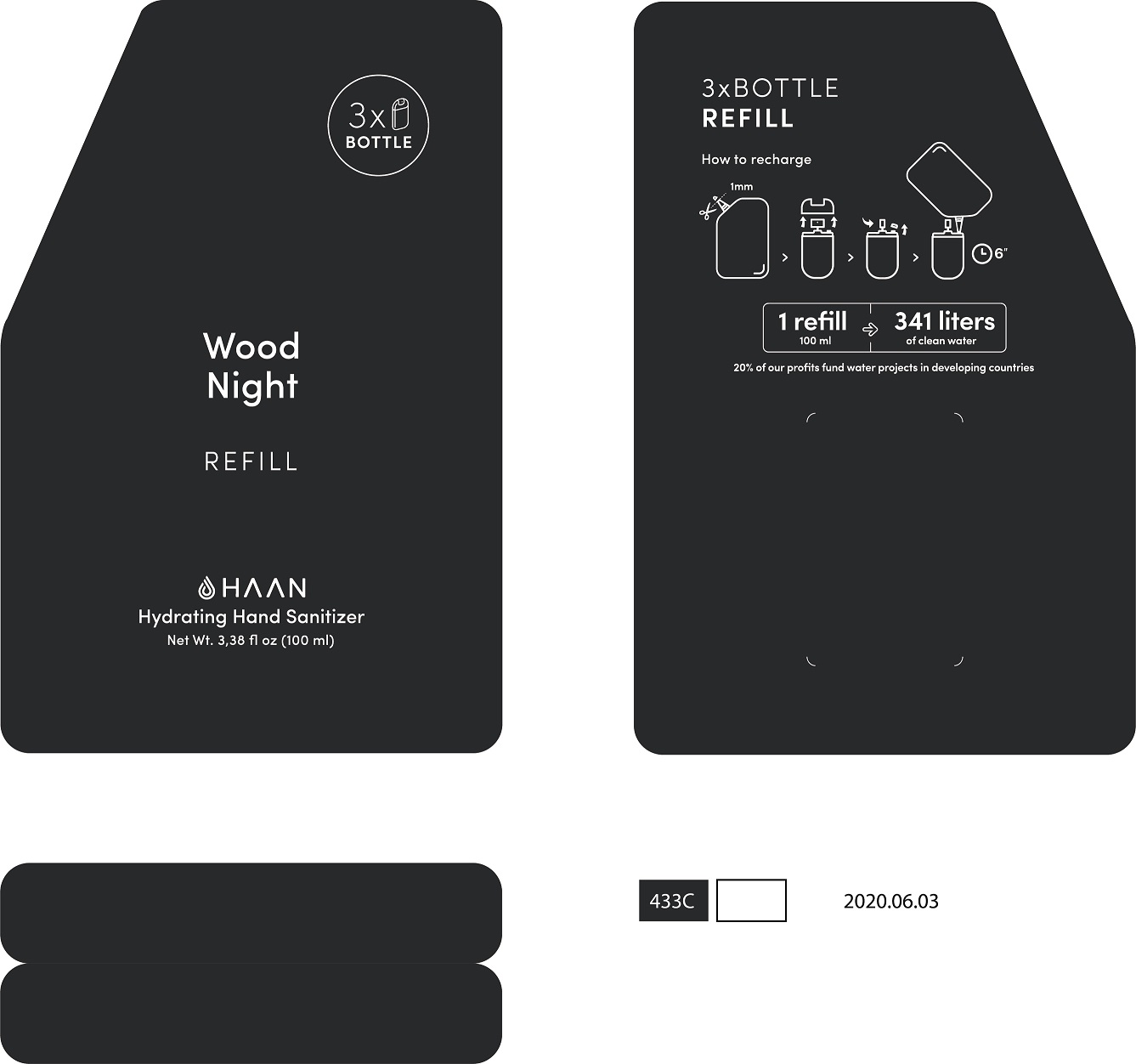 DRUG LABEL: Hand Sanitizer Refill
NDC: 79091-014 | Form: LIQUID
Manufacturer: HAAN BRAND SL
Category: otc | Type: HUMAN OTC DRUG LABEL
Date: 20241008

ACTIVE INGREDIENTS: ALCOHOL 70 mg/1 mL
INACTIVE INGREDIENTS: METHYL GLUCETH-10; WATER; BENZYL BENZOATE; ALOE VERA LEAF; SODIUM BENZOATE; POTASSIUM SORBATE; ISOMETHYL-.ALPHA.-IONONE; BUTYL ACRYLATE/C16-C20 ALKYL METHACRYLATE/METHACRYLIC ACID/METHYL METHACRYLATE COPOLYMER; .ALPHA.-HEXYLCINNAMALDEHYDE; TROMETHAMINE

Hand Sanitizer

Uses

* To decrease bacterias on the hand. Recommended for repeated use.

Active Ingredient

Active Ingredient Purpose

- Ethyl Alcohol 65%...................................Antiseptic

Warnings

- For external use only- hands
- When using this product keep out o f eyes. In case of contact, flush throughly with water.
- Do Not Inhale or ingest.
- Avoid contact with broken skin
- Keep out of reach of children. In case of incidental ingestion seek professional assistance or contact a Poison Control Center inmediately.
- Stop use and ask Doctor: if skin irritation develops.
- Flammable: Keep away from heat and flame.

Stop use and ask a doctor if

* Irritation develops

Keep out of reach of children. In case of incidental ingestion, see professional advice or contact a Poison Control Center inmediately.

Directions

Directions: Wet hands throughly with product and allow to dry without wiping

- For Children under 6 years of age do not use without supervision of an adult. Not recomended for infants

Inactive Ingredients

Water, Methyl Gluceth-10, C10-30 Alkyl Acrylate Crosspolymer, Parfum(Fragrance), Tromethamine, Potassium Sorbate, Sodium Benzoate, Benzyl Benzoate, Alpha Isomethyl Ionone

Questions?

QUESTIONS OR COMMENTS: Visit Haanready.com

Uses

* To decrease bacterias on the hand. Recommended for repeated use.